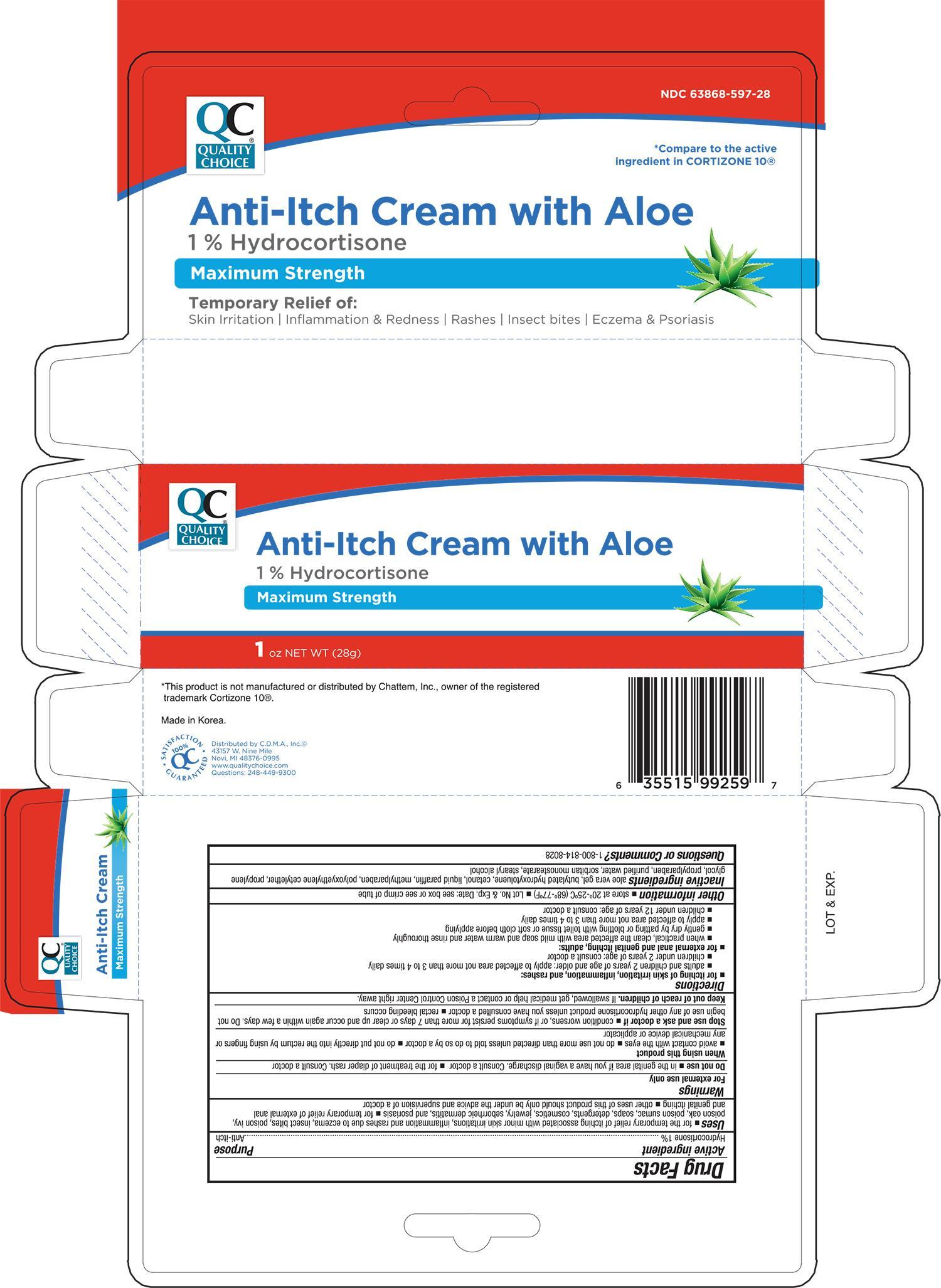 DRUG LABEL: Quality Choice Anti Itch with Aloe
NDC: 63868-597 | Form: OINTMENT
Manufacturer: Chain Drug Marketing Association Inc
Category: otc | Type: HUMAN OTC DRUG LABEL
Date: 20191209

ACTIVE INGREDIENTS: HYDROCORTISONE 1 g/100 g
INACTIVE INGREDIENTS: ALOE VERA LEAF; BUTYLATED HYDROXYTOLUENE; PARAFFIN; METHYLPARABEN; PROPYLENE GLYCOL; PROPYLPARABEN; WATER; SORBITAN MONOSTEARATE; STEARYL ALCOHOL

QC Anti-itch Cream with Aloe 1oz 99259, 2019

Active ingredient Purpose

Hydrocortisone 1%................................................... Anti-itch

Uses

- for the temporary relief of itching associated with minor skin irritations, inflammation and rashes due to eczema, insect bites, poison ivy, poison sumac, soaps, detergents, cosmetics, jewelry, seborrheic dermatitis, and psoriasis
- for temporary relief of external anal and genital itching
- other uses of this product should only be under the advice and supervision of a doctor

Warnings

For external use only

Do not use

- in the genital area if you have a vaginal discharge. Consult a doctor
- for the treatment of diaper rash. Consult a doctor

When using this product

- avoid contact with the eyes
- do not use more than directed unless told to do so by a doctor
- do not put directly into the rectum by using fingers or any mechanical device or applicator

Stop use and ask a doctor if

- condition worsens, or if symptoms persist for more than 7 days or clear up and occur again within a few days. Do not begin use of any other hydrocortisone product unless you have consulted a doctor
- rectal bleeding occurs

Keep out of reach of children

If swallowed, get medical help or contact a Poison Control Center right away.

Directions

- for itching of skin irritation, inflammation, and rashes:
- adults and children 2 years of age and older: apply to affected area not more than 3 to 4 times daily
- children under 2 years of age: consult a doctor
- for external anal and genital itching, adults:
- when practical, clean the affected area with mild soap and warm water and rinse thoroughly
- gently dry by patting or blotting with toilet tissue or soft cloth before applying
- apply to affected area not more than 3 to 4 times daily
- children under 12 years of age: consult a doctor

Other information

- store at 20°-25°C (68°-77°F)
- Lot No. & Exp. Date: see box or see crimp of tube

Inactive ingredients

aloe vera gel, butylated hydroxytoluene, cetanol, liquid paraffin, methylparaben, polyoxyethylene cetyether, propylene glycol, propylparaben, purified water, sorbitan monostearate, stearyl alcohol

DOSAGE AND ADMINISTRATION

DISTRIBUTED BY C.D.M.A., INC.

43157 W. NINE MILE

NOVI, MI 48376-0995

www.qualitychoice.com

MADE IN KOREA